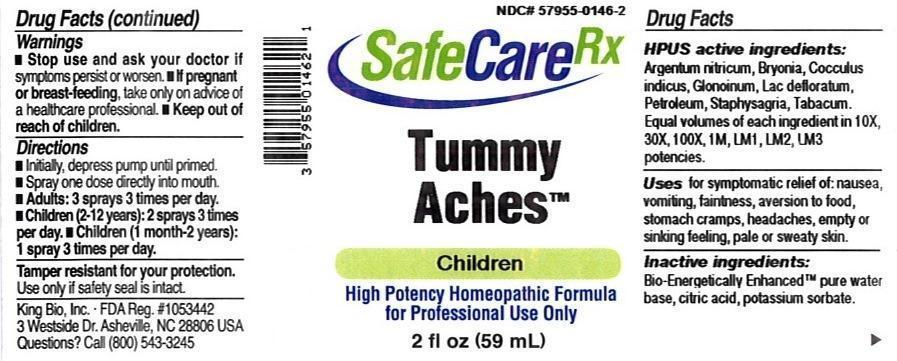 DRUG LABEL: Tummy Aches
NDC: 57955-0146 | Form: LIQUID
Manufacturer: King Bio Inc.
Category: homeopathic | Type: HUMAN OTC DRUG LABEL
Date: 20150327

ACTIVE INGREDIENTS: SILVER NITRATE 10 [hp_X]/59 mL; BRYONIA ALBA ROOT 10 [hp_X]/59 mL; ANAMIRTA COCCULUS SEED 10 [hp_X]/59 mL; NITROGLYCERIN 10 [hp_X]/59 mL; SKIM MILK 10 [hp_X]/59 mL; KEROSENE 10 [hp_X]/59 mL; DELPHINIUM STAPHISAGRIA SEED 10 [hp_X]/59 mL; TOBACCO LEAF 10 [hp_X]/59 mL
INACTIVE INGREDIENTS: WATER; ANHYDROUS CITRIC ACID; POTASSIUM SORBATE

Tummy Aches™

ACTIVE INGREDIENT

Drug Facts__________________________________________________________________________________________________________

HPUS activeingredients: Argentum nitricum, Bryonia, Cocculus indicus, Glonoinum, Lac defloratum, Petroleum, Staphysagria, Tabacum. Equal volumes of each ingredient in 10X, 30X, 100X, 1M, LM1, LM2, LM3 potencies.

INDICATIONS AND USAGE

Uses for symptomatic relief of: nausea, vomiting, faintness, aversion to food, stomach cramps, headaches, empty or sinking feeling, pale or sweaty skin.

Inactive Ingredients:

Bio-Energetically Enhanced™ pure water, citric acid and potassium sorbate.

Warnings

- Stop use and ask your doctor if symptoms persist or worsen.
- If pregnant or breast-feeding, take only on advice of a healthcare professional.

- Keep out of reach of children.

Directions

- Initially, depress pump until primed.
- Spray one dose directly into mouth.
- Adults: 3 sprays 3 times per day.
- Children (2-12 years): 2 sprays 3 times per day.
- Children (1 month-2 years): 1 spray 3 times per day.

OTHER SAFETY INFORMATION

Tamper resistant for your protection. Use only if safety seal is intact.

PURPOSE

Uses for symptomatic relief of:

- nausea
- vomiting
- faintness
- aversion to food
- stomach cramps
- headaches
- empty or sinking feeling
- pale or sweaty skin